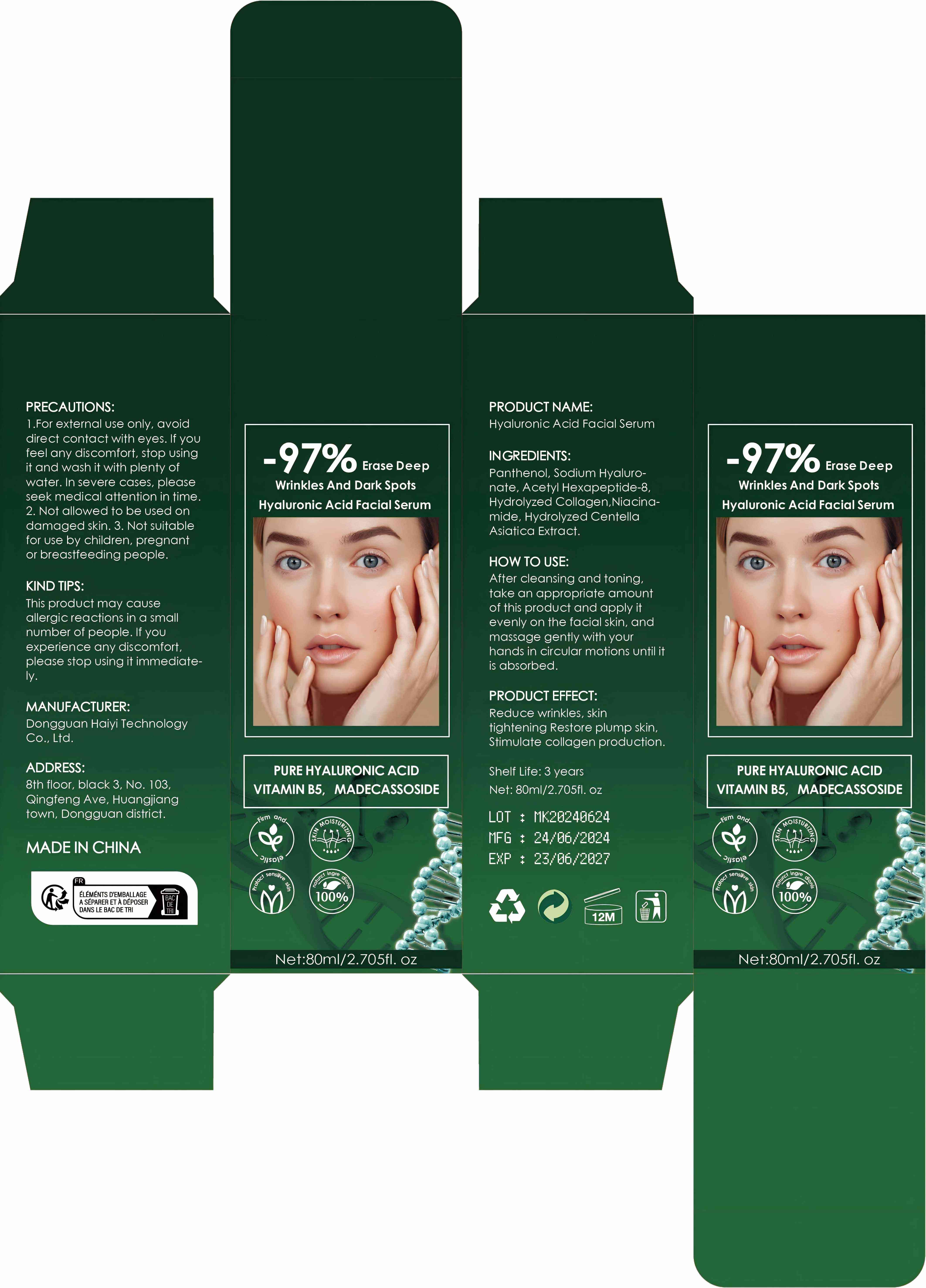 DRUG LABEL: Hyaluronic Acid Facial Serum
NDC: 84732-053 | Form: LIQUID
Manufacturer: Dongguan Haiyi Technology Co.,Ltd.
Category: otc | Type: HUMAN OTC DRUG LABEL
Date: 20241017

ACTIVE INGREDIENTS: PANTHENOL 1 mg/80 mL
INACTIVE INGREDIENTS: NIACINAMIDE; ACETYL HEXAPEPTIDE-8; PENICILLOYL POLYLYSINE; PEG-9 DIGLYCIDYL ETHER/SODIUM HYALURONATE CROSSPOLYMER; CENTELLA ASIATICA TRITERPENOIDS

Active ingredient

Panthenol

Inactive ingredient

Sodium Hyaluronate, Acetyl Hexapeptide-8，Hydrolyzed Collagen,Niacinamide, Hydrolyzed Centella Asiatica Extract.

Purpose section

Reduce wrinkles, skintightening Restore plump skin.Stimulate collagen production.

Warning

This product may causeallergic reactions in a small number of people.

lf you experience any discomfort.please stop using it immediately

not use

Not suitable for use by children, pregnantor breast feeding people.

OUT OF CHILDREN

KEEP THE PRODUCT OUT OF REACH OF CHILDREN to

HOW TO USE

After cleansing and toning,take an appropriate amountof this product and apply it evenly on the facial skin, and massage gently with your hands in circular motions until it is absorbed

Dosage

take an appropriateamount,Use 2-3 times a week